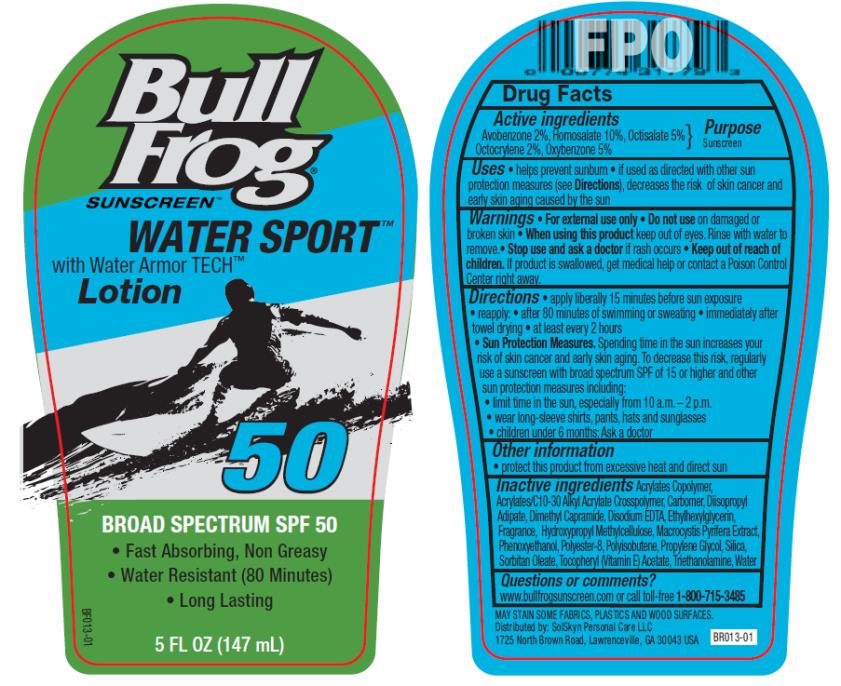 DRUG LABEL: BullFrog SPF50 Water Sport
NDC: 70281-324 | Form: LOTION
Manufacturer: SolSkyn Personal Care LLC
Category: otc | Type: HUMAN OTC DRUG LABEL
Date: 20180216

ACTIVE INGREDIENTS: AVOBENZONE 2 mg/100 mg; HOMOSALATE 10 mg/100 mg; OCTISALATE 5 mg/100 mg; OCTOCRYLENE 2 mg/100 mg; OXYBENZONE 5 mg/100 mg
INACTIVE INGREDIENTS: BUTYL ACRYLATE/METHYL METHACRYLATE/METHACRYLIC ACID COPOLYMER (18000 MW); CARBOMER INTERPOLYMER TYPE A (55000 CPS); CARBOMER COPOLYMER TYPE A; POLYISOBUTYLENE (1300 MW); DIISOPROPYL ADIPATE; DIMETHYL CAPRAMIDE; EDETATE DISODIUM ANHYDROUS; ETHYLHEXYLGLYCERIN; HYPROMELLOSES; MACROCYSTIS PYRIFERA; PHENOXYETHANOL; POLYESTER-8 (1400 MW, CYANODIPHENYLPROPENOYL CAPPED); PROPYLENE GLYCOL; SILICON DIOXIDE; SORBITAN MONOOLEATE; .ALPHA.-TOCOPHEROL; TROLAMINE; WATER

BF Water Sport SPF50 Lotion

BullFrog SPF50 Water Sport Lotion

Active Ingredients

Avobenzone 2%, Homosalate 10%, Octisalate 5%, Octocrylene 2%, Oxybenzone 5%

Purpose

Sunscreen

Uses

- helps prevent sunburn
- if used as directed with other sun protection measures (see Directions), decreases the risk of skin cancer and early skin aging caused by the sun

Warnings

- For external use only
- Flammable: keep away from fire or flame.

Do not use

on damaged or broken skin.

When using this product keep out of eyes.

Rinse with water to remove.

Keep out of reach of children.

If product is swallowed, get medical help or contact a Poison Control Center right away.

Directions

- apply liberally 15 minutes before sun exposure
- re-apply:
  • after 80 minutes of swimming or sweating
  • immediately after towel drying
  • at least every 2 hours

Sun Protection Measures. Spending time in the sun increases your risk of skin cancer and early skin aging. To decrease this risk, regularly use a sunscreen with broad spectrum SPF of 15 or higher and other sun protection measures including:

- limit time in the sun, especially from 10 a.m.-2 p.m.
- wear long-sleeved shirts, pants, hats and sunglasses
- children under 6 months: ask a doctor

Other information

- protect this product from excessive heat and direct sun

Inactive Ingredients

Acrylates Copolymer, Acrylates/C10-30 Alkyl Acrylate Crosspolymer, Carbomer, Diisopropyl Adipate, Dimethyl Capramide, Disodium EDTA, Ethylhexylglycerin, Fragrance, Hydroxypropyl Methylcellulose, Macrocystis Pyrifera Extract, Phenoxyethanol, Polyester-8, Polyisobutene, Propylene Glycol, Silica, Sorbitan Oleate, Tocopheryl (Vitamin E) Acetate, Triethanolamine, Water

Questions or comments?

www.bullfrogsunscreen.com or call toll-free 1-800-715-3485

MAY STAIN SOME FABRICS, PLASTICS AND WOOD SURFACES.

PRINCIPAL DISPLAY PANEL

BULL
FROG
SUNSCREEN
WATER SPORT
with Water Armor TECH
Lotion
50
BROAD SPECTRUM SPF 50
5 FL OZ (147 mL)